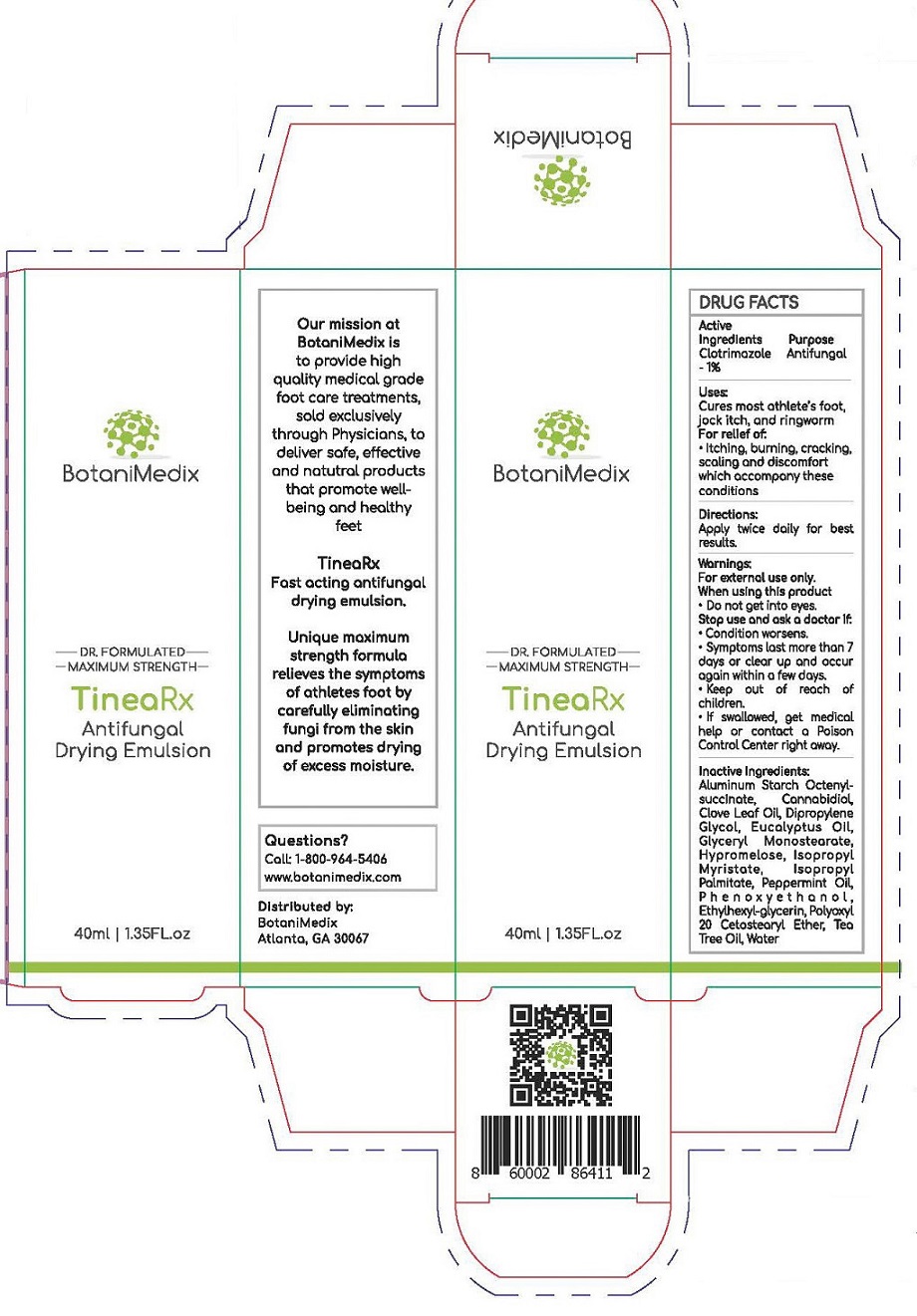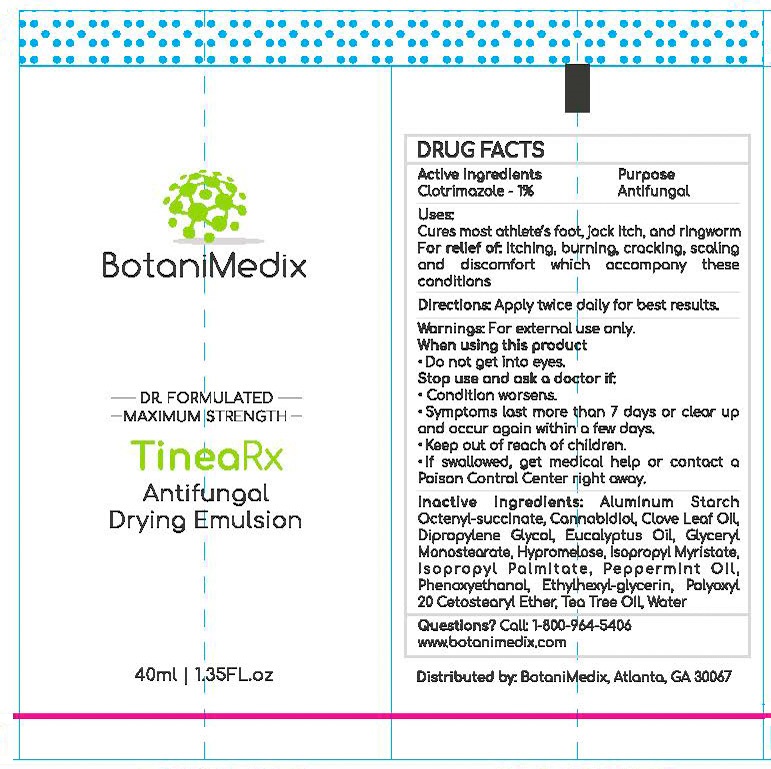 DRUG LABEL: Botanimedix TineaRX Antifungal Drying Emulsion
NDC: 52261-5801 | Form: CREAM
Manufacturer: Cosco International, Inc.
Category: otc | Type: HUMAN OTC DRUG LABEL
Date: 20200130

ACTIVE INGREDIENTS: CLOTRIMAZOLE 0.01 kg/1 kg
INACTIVE INGREDIENTS: ISOPROPYL PALMITATE; GLYCERYL MONOSTEARATE; POLYOXYL 20 CETOSTEARYL ETHER; PEPPERMINT OIL; ALUMINUM STARCH OCTENYLSUCCINATE; ISOPROPYL MYRISTATE; HYPROMELLOSE 2208 (15000 MPA.S); WATER; TEA TREE OIL; EUCALYPTUS OIL; PHENOXYETHANOL; ETHYLHEXYLGLYCERIN; CANNABIDIOL; CLOVE LEAF OIL; DIPROPYLENE GLYCOL

Botanimedix TineaRX Antifungal Drying Emulsion

DRUG FACTS

Active Ingredient Purpose
Clotrimazole 1%........................Anti-fungal

Uses:

Cures most athlete's foot, jock itch, and ring worm

INDICATIONS AND USAGE

For relief of:

- Itching, burning, cracking, scaling, and discomfort which accompany these conditions.

Directions:

Apply twice daily for best results.

Warnings:

For external use only.

When using this product

- Do not get into eyes.

Stop use and ask a doctor if:

- Condition worsens.
- Symptoms last more than 7 days or clear and occur again within a few days.

- Keep out of reach of children.
- If swallowed, get medical help or contact a Poison Control Center right away.

Inactive Ingredients:

Aluminum Starch Octenylsuccinate, Cannabidiol, Clove Leaf Oil, Dipropylene Glycol, Eucalyptus Oil, Glyceryl Monostearate, Hypromellose, Isopropyl Myristate, Isopropyl Palmitate, Peppermint Oil, Phenoxyethanol, Ethylhexylglycerin, Polyoxyl 20 Cetostearyl Ether, Tea Tree Oil, Water

Questions?

Call: 1-800-964-5406

www.botanimedix.com